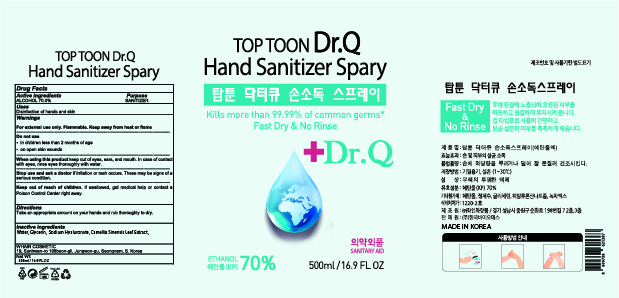 DRUG LABEL: TOP TOON Dr.Q Hand SanitizerSpray
NDC: 73823-202 | Form: SPRAY
Manufacturer: WHAIN COSMETIC
Category: otc | Type: HUMAN OTC DRUG LABEL
Date: 20210120

ACTIVE INGREDIENTS: ALCOHOL 350 mL/500 mL
INACTIVE INGREDIENTS: WATER; GREEN TEA LEAF; GLYCERIN; HYALURONATE SODIUM

[WHAIN COSMETIC] TOP TOON Dr.Q Hand Sanitizer Spray
73823-202-01